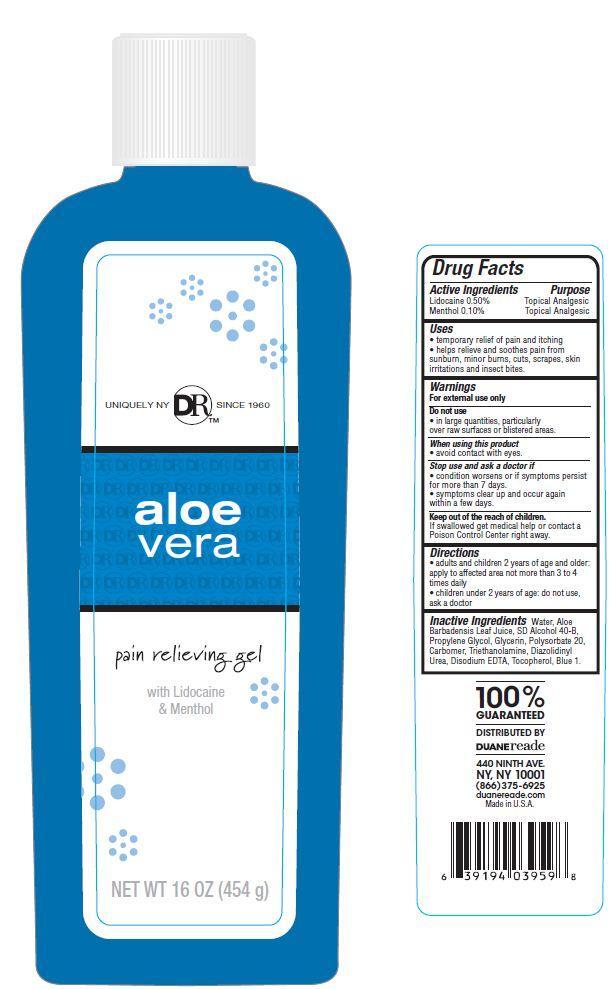 DRUG LABEL: Duane Reade Aloe Vera
NDC: 67732-408 | Form: GEL
Manufacturer: DUANE READE INC.
Category: otc | Type: HUMAN OTC DRUG LABEL
Date: 20121114

ACTIVE INGREDIENTS: LIDOCAINE 0.5 g/100 g; MENTHOL 0.10 g/100 g
INACTIVE INGREDIENTS: WATER; TROLAMINE; TOCOPHEROL; EDETATE DISODIUM; ALOE VERA LEAF; PROPYLENE GLYCOL; GLYCERIN; POLYSORBATE 20; DIAZOLIDINYL UREA

Drug Facts

Active Ingredients

Lidocaine 0.50%
Menthol 0.10%

Purpose

Topical Analgesic

Uses

- temporary relief of pain and itching
- helps relieve and soothes pain from sunburn, minor burns, cuts, scrapes, skin irritations and insect bites.

Warnings

For external use only

Do not use

- in large quantities, particularly over raw surfaces or blistered areas.

When using this product

- avoid contact with eyes.

stop use and ask a doctor if

- conditions worsens or if symptoms persists for more than 7 days.
- symptoms clear up and occur again within a few days.

Keep out of the reach of children.

If swallowed get medical help or contact a Poison Control Center right away.

Directions

- adults and children 2 years of age and older.apply to affected area not more than 3 to 4 times daily
- children under 2 years of age: do not use, ask a doctor.

Inactive Ingredients

Water, Aloe Barbadensis Leaf Juice, SD Alcohol 40-B, Propylene Glycol, Glycerin, Polysorbate 20, Carbomer, Triethanolamine, Diazolidinyl urea, Disodium EDTA, Tocopherol, Blue 1.

Principal Display Panel

UNIQUELY NY DRTM SINCE 1960

aloe
vera
pain relieving gel
with Lidocaine and Menthol
NET WT 16 OZ (454 g)